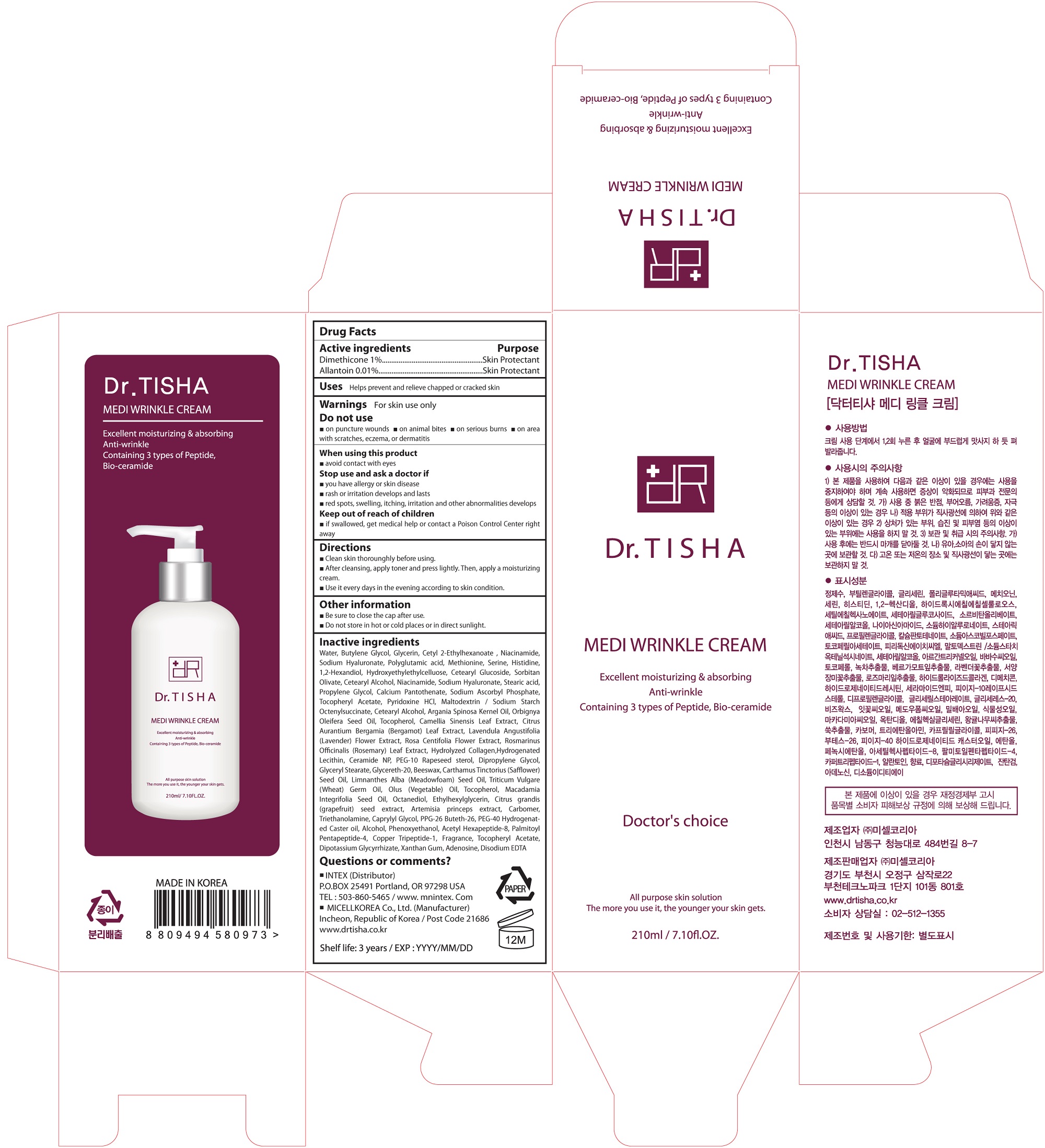 DRUG LABEL: Medi Wrinkle Cream
NDC: 71327-004 | Form: CREAM
Manufacturer: MICELL KOREA CO.,LTD
Category: otc | Type: HUMAN OTC DRUG LABEL
Date: 20170323

ACTIVE INGREDIENTS: Dimethicone 0.0021 g/210 mL; Allantoin 0.000021 g/210 mL
INACTIVE INGREDIENTS: Water; Methionine; Serine; Histidine; Butylene Glycol; Propylene Glycol; Maltodextrin

ACTIVE INGREDIENT

Dimethicone (1%) - Skin Protectact
Allantoin (0.01%) - Skin Protectact

INACTIVE INGREDIENT

Water, Butylene Glycol, Glycerin, Cetyl 2-Ethylhexanoate , Niacinamide, Sodium Hyaluronate, Polyglutamic acid, Methionine, Serine, Histidine, 1,2-Hexandiol, Hydroxyethylethylcelluose, Cetearyl Glucoside, Sorbitan Olivate, Cetearyl Alcohol, Niacinamide, Sodium Hyaluronate, Stearic acid, Propylene Glycol, Calcium Pantothenate, Sodium Ascorbyl Phosphate, Tocopheryl Acetate, Pyridoxine HCl, Maltodextrin / Sodium Starch Octenylsuccinate, Cetearyl Alcohol, Argania Spinosa Kernel Oil, Orbignya Oleifera Seed Oil, Tocopherol, Camellia Sinensis Leaf Extract, Citrus Aurantium Bergamia (Bergamot) Leaf Extract, Lavendula Angustifolia (Lavender) Flower Extract, Rosa Centifolia Flower Extract, Rosmarinus Officinalis (Rosemary) Leaf Extract, Hydrolyzed Collagen,Hydrogenated Lecithin, Ceramide NP, PEG-10 Rapeseed sterol, Dipropylene Glycol, Glyceryl Stearate, Glycereth-20, Beeswax, Carthamus Tinctorius (Safflower) Seed Oil, Limnanthes Alba (Meadowfoam) Seed Oil, Triticum Vulgare (Wheat) Germ Oil, Olus (Vegetable) Oil, Tocopherol, Macadamia Integrifolia Seed Oil, Octanediol, Ethylhexylglycerin, Citrus grandis (grapefruit) seed extract, Artemisia princeps extract, Carbomer, Triethanolamine, Caprylyl Glycol, PPG-26 Buteth-26, PEG-40 Hydrogenated Caster oil, Alcohol, Phenoxyethanol, Acetyl Hexapeptide-8, Palmitoyl Pentapeptide-4, Copper Tripeptide-1, Fragrance, Tocopheryl Acetate, Dipotassium Glycyrrhizate, Xanthan Gum, Adenosine, Disodium EDTA

PURPOSE

Skin Protectact

WARNINGS

For skin use only.
Do not use
 on puncture wounds  on animal bites  on serious burns  on area with scratches, eczema, or dermatitis
When using this product
 avoid contact with eyes
Stop use and ask a doctor if
 you have allergy or skin disease
 rash or irritation develops and lasts
 red spots, swelling, itching, irritation and other abnormalities develops

KEEP OUT OF REACH OF CHILDREN

 if swallowed, get medical help or contact a Poison Control Center right away

INDICATIONS & USAGE

 Clean skin thorounghly before using
 After cleansing, apply toner and press lightly. Then, apply a moisturizing cream
 Use it every days in the evening according to skin condition

DOSAGE & ADMINISTRATION

 Clean skin thorounghly before using
 After cleansing, apply toner and press lightly. Then, apply a moisturizing cream
 Use it every days in the evening according to skin condition